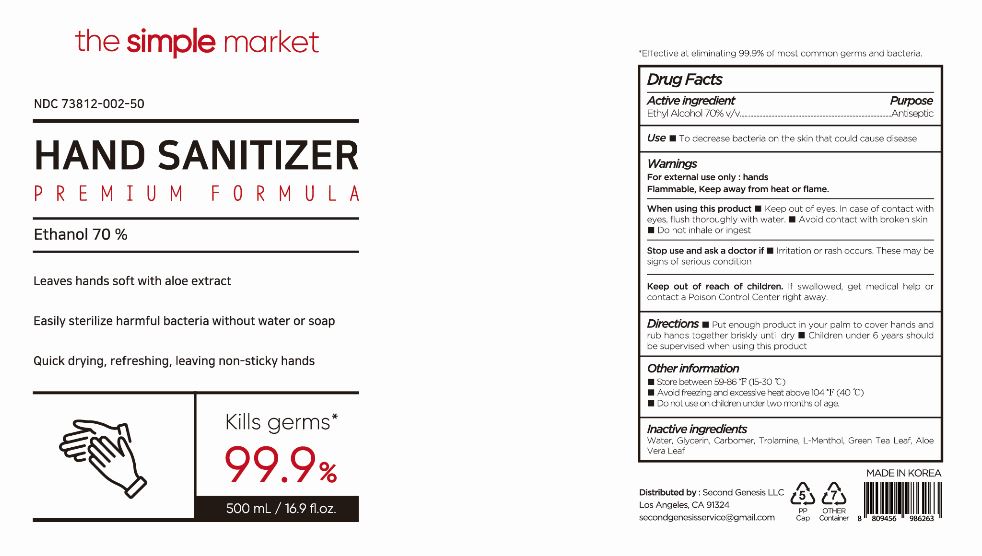 DRUG LABEL: HAND SANITIZER PREMIUM FORMULA
NDC: 73812-002 | Form: GEL
Manufacturer: LTP Global
Category: otc | Type: HUMAN OTC DRUG LABEL
Date: 20200608

ACTIVE INGREDIENTS: ALCOHOL 70 mL/100 mL
INACTIVE INGREDIENTS: ALOE VERA LEAF; TROLAMINE; LEVOMENTHOL; GLYCERIN; CARBOMER HOMOPOLYMER TYPE B (ALLYL PENTAERYTHRITOL CROSSLINKED); WATER; GREEN TEA LEAF

Active Ingredient(s)

Alcohol 70% v/v. Purpose: Antiseptic

Purpose

Antiseptic

Use

- to decrease bacteria that potentially can cause disease
- recommended for repeated use

Warnings

For external use only : hands

Flammable. Keep away from heat or flame.

- When using this product keep out of eyes. In case of contact with eyes, flush thoroughly with water.
- avoid contact with broken skin
- do not inhale or ingest

Stop use and ask a doctor if

- irritation and redness develop
- condition persists for more than 72 hours

Keep out of reach of children. If swallowed, get medical help or contact a Poison Control Center right away.

Directions

- wet hands thoroughly with product and allow to dry without wiping
- for children under 6, use only under adult supervision
- not recommened for infacts

Other information

- Store between 15-30C (59-86F)
- Avoid freezing and excessive heat above 40C (104F)
- Do not use on children under two months of age.

Inactive ingredients

Water, Glycerin, Carbomer, Trolamine, L-Menthol, Green Tea Leaf, Aloe Vera Leaf